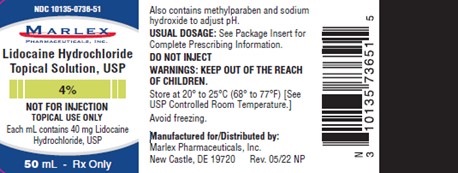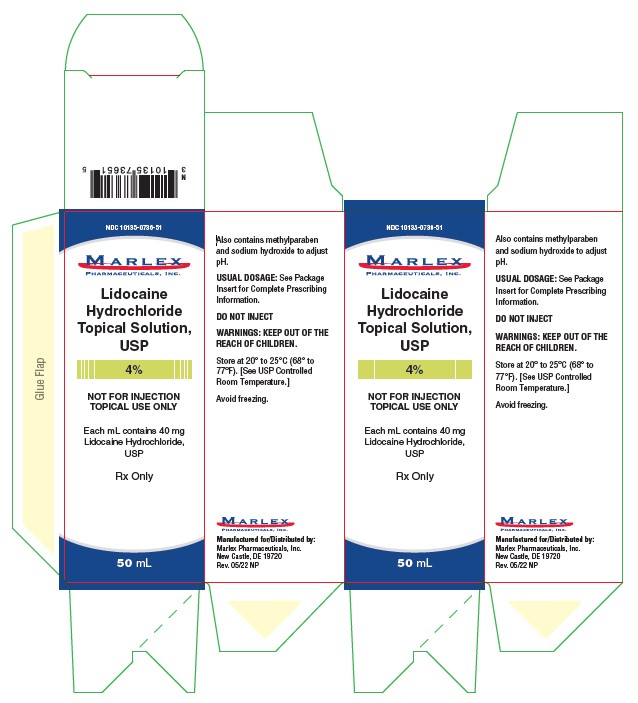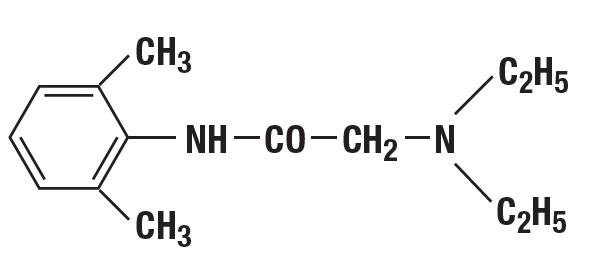 DRUG LABEL: Lidocaine Hydrochloride
NDC: 10135-736 | Form: SOLUTION
Manufacturer: Marlex Pharmaceuticals, Inc.
Category: prescription | Type: HUMAN PRESCRIPTION DRUG LABEL
Date: 20251030

ACTIVE INGREDIENTS: LIDOCAINE HYDROCHLORIDE 40 mg/1 mL
INACTIVE INGREDIENTS: METHYLPARABEN; SODIUM HYDROXIDE; WATER

Lidocaine Hydrochloride Topical Solution, USP
Rx only

DESCRIPTION

Lidocaine Hydrochloride Topical Solution, USP contains a local anesthetic agent and is administered topically. See INDICATIONS for specific uses.

Each mL contains:

Lidocaine Hydrochloride, USP ................................................................................... 40 mg

Methylparaben, Sodium Hydroxide (to adjust pH) in an aqueous solution. NOT FOR INJECTION.

Lidocaine is a local anesthetic chemically designated as 2-(diethylamino)-N-(2,6-dimethyl-phenyl)-acetamide. It has the following structural formula:

CLINICAL PHARMACOLOGY

Mechanism of Action

Lidocaine stabilizes the neuronal membrane by inhibiting the ionic fluxes required for the initiation and conduction of impulses, thereby effecting local anesthetic action.

Hemodynamics

Excessive blood levels may cause changes in cardiac output, total peripheral resistance, and mean arterial pressure. These changes may be attributable to a direct depressant effect of the local anesthetic agent on various components of the cardiovascular system.

Pharmacokinetics and Metabolism

Lidocaine may be absorbed following topical administration to mucous membranes, its rate of absorption and percent of dose absorbed depending upon concentration and total dose administered, the specific site of application, and duration of exposure. In general, the rate of absorption of local anesthetic agents following topical application occurs most rapidly after intratracheal administration. Lidocaine is also well-absorbed from the gastrointestinal tract, but little intact drug appears in the circulation because of biotransformation in the liver.

Lidocaine is metabolized rapidly by the liver, and metabolites and unchanged drug are excreted by the kidneys. Biotransformation includes oxidative N-dealkylation, ring hydroxylation, cleavage of the amide linkage, and conjugation. N-dealkylation, a major pathway of biotransformation, yields the metabolites monoethylglycinexylidide and glycinexylidide. The pharmacological/toxicological actions of these metabolites are similar to, but less potent than, those of lidocaine. Approximately 90% of lidocaine administered is excreted in the form of various metabolites, and less than 10% is excreted unchanged. The primary metabolite in urine is a conjugate of 4-hydroxy-2,6-dimethylaniline.

The plasma binding of lidocaine is dependent on drug concentration, and the fraction bound decreases with increasing concentration. At concentrations of 1 to 4 mcg of free base per ml, 60 to 80 percent of lidocaine is protein bound. Binding is also dependent on the plasma concentration of the alpha-1-acid glycoprotein.

Lidocaine crosses the blood-brain and placental barriers, presumably by passive diffusion.

Studies of lidocaine metabolism following intravenous bolus injections have shown that the elimination half-life of this agent is typically 1.5 to 2 hours. Because of the rapid rate at which lidocaine is metabolized, any condition that affects liver function may alter lidocaine kinetics. The half-life may be prolonged two-fold or more in patients with liver dysfunction. Renal dysfunction does not affect lidocaine kinetics but may increase the accumulation of metabolites.

Factors such as acidosis and the use of CNS stimulants and depressants affect the CNS levels of lidocaine required to produce overt systemic effects. Objective adverse manifestations become increasingly apparent with increasing venous plasma above 6 mcg free base per ml. In the rhesus monkey arterial blood levels of 18-21 mcg/mL have been shown to be threshold for convulsive activity.

INDICATIONS

Lidocaine hydrochloride is indicated for the production of topical anesthesia of accessible mucous membranes of the oral and nasal cavities and proximal portions of the digestive tract.

CONTRAINDICATIONS

Lidocaine hydrochloride is contraindicated in patients with a known hypersensitivity either to local anesthetics of the amide type or to the components of the topical solution.

WARNINGS

IN ORDER TO MANAGE POSSIBLE ADVERSE REACTIONS, RESUSCITATIVE EQUIPMENT, OXYGEN AND OTHER RESUSCITATIVE DRUGS MUST BE IMMEDIATELY AVAILABLE WHEN LOCAL ANESTHETIC AGENTS, SUCH AS LIDOCAINE, ARE ADMINISTERED TO MUCOUS MEMBRANES.

Lidocaine hydrochloride should be used with extreme caution if there is sepsis or severely traumatized mucosa in the area of application, since under such conditions there is the potential for rapid systemic absorption.

Methemoglobinemia

Cases of methemoglobinemia have been reported in association with local anesthetic use. Although all patients are at risk for methemoglobinemia, patients with glucose-6-phosphate dehydrogenase deficiency, congenital or idiopathic methemoglobinemia, cardiac or pulmonary compromise, infants under 6 months of age, and concurrent exposure to oxidizing agents or their metabolites are more susceptible to developing clinical manifestations of the condition. If local anesthetics must be used in these patients, close monitoring for symptoms and signs of methemoglobinemia is recommended.

Signs and symptoms of methemoglobinemia may occur immediately or may be delayed some hours after exposure, and are characterized by a cyanotic skin discoloration and abnormal coloration of the blood. Methemoglobin levels may continue to rise; therefore, immediate treatment is required to avert more serious central nervous system and cardiovascular adverse effects, including seizures, coma, arrhythmias, and death. Discontinue lidocaine and any other oxidizing agents. Depending on the severity of the symptoms, patients may respond to supportive care, i.e., oxygen therapy, hydration. More severe symptoms may require treatment with methylene blue, exchange transfusion, or hyperbaric oxygen.

PRECAUTIONS

GENERAL

The safety and effectiveness of lidocaine depend on proper dosage, correct technique, adequate precautions, and readiness for emergencies. Resuscitative equipment, oxygen, and other resuscitative drugs should be available for immediate use. (See WARNINGS and ADVERSE REACTIONS). The lowest dosage that results in effective anesthesia should be used to avoid high plasma levels and serious adverse effects. Repeated doses of lidocaine may cause significant increases in blood levels with each repeated dose because of slow accumulation of the drug and/or its metabolites. Tolerance to elevated blood levels varies with the status of the patient. Debilitated, elderly patients, acutely ill patients, and children should be given reduced doses commensurate with their age and physical status. Lidocaine should also be used with caution in patients with severe shock or heart block.

Lidocaine hydrochloride should be used with caution in patients with known drug sensitivities. Patients allergic to para-aminobenzoic acid derivatives (procaine, tetracaine, benzocaine, etc.) have not shown cross sensitivity to lidocaine.

Although it has been shown that the rate of absorption of lidocaine after spraying the laryngotracheal mucosa with a solution of the local anesthetic agent is normally relatively slow, there is the attendant risk that occasionally some of the solution may gravitate into the lower respiratory tract where surface area for absorption and tissue blood flow are markedly greater. This can result in unexpectedly rapid and high blood levels, and this possibility must be kept in mind whenever lidocaine hydrochloride topical solution is administered.

Many drugs used during the conduct of anesthesia are considered potential triggering agents for familial malignant hyperthermia. Since it is not known whether amide-type local anesthetics may trigger this reaction and since the need for supplemental general anesthesia cannot be predicted in advance, it is suggested that a standard protocol for management should be available. Early unexplained signs of tachycardia, tachypnea, labile blood pressure and metabolic acidosis may precede temperature elevation. Successful outcome is dependent on early diagnosis, prompt discontinuance of the suspect triggering agent(s) and institution of treatment, including oxygen therapy, indicated supportive measures and dantrolene (consult dantrolene sodium intravenous package insert before using).

INFORMATION FOR PATIENTS

Inform patients that use of local anesthetics may cause methemoglobinemia, a serious condition that must be treated promptly. Advise patients or caregivers to stop use and seek immediate medical attention if they or someone in their care experience the following signs or symptoms: pale, gray, or blue colored skin (cyanosis); headache; rapid heart rate; shortness of breath; lightheadedness; or fatigue.

When topical anesthetics are used in the mouth or throat, the patient should be aware that the production of topical anesthesia may impair swallowing and thus enhance the danger of aspiration. For this reason, food should not be ingested for 60 minutes following use of local anesthetic preparations in the mouth or throat area. This is particularly important in children because of their frequency of eating.

Numbness of the tongue or buccal mucosa may increase the danger of unintentional biting trauma. Food and chewing gum should not be taken while the mouth or throat area is anesthetized.

DRUG INTERACTIONS

Patients that are administered local anesthetics may be at increased risk of developing methemoglobinemia when concurrently exposed to the following oxidizing agents:

Class | Examples
Nitrates/Nitrites | nitroglycerin, nitroprusside, nitric oxide, nitrous oxide
Local anesthetics | benzocaine, lidocaine, bupivacaine, mepivacaine, tetracaine, prilocaine, procaine, articaine
Antineoplastic agents | cyclophosphamide, flutamide, rasburicase, isofamide, hydroxyurea
Antibiotics | dapsone, sulfonamides, nitrofurantoin, para-aminosalicylic acid
Antimalarials | chloroquine, primaquine
Anticonvulsants | phenytoin, sodium valproate, phenobarbital
Other drugs | acetaminophen, metoclopramide, sulfa drugs (i.e., sulfasalazine), quinine

CARCINOGENESIS & MUTAGENESIS & IMPAIRMENT OF FERTILITY

Studies of lidocaine in animals to evaluate the carcinogenic and mutagenic potential or the effect on fertility have not been conducted.

USE IN PREGNANCY

Reproduction studies have been performed in rats at doses up to 6.6 times the human dose and have revealed no evidence of harm to the fetus caused by lidocaine. There are, however, no adequate and well-controlled studies in pregnant women. Animal reproduction studies are not always predictive of human response. General consideration should be given to this fact before administering lidocaine to women of childbearing potential, especially during early pregnancy when maximum organogenesis takes place.

LABOR & DELIVERY

Lidocaine is not contraindicated in labor and delivery. Should lidocaine hydrochloride topical solution be used concomitantly with other products containing lidocaine, the total dose being administered must be kept in mind.

NURSING MOTHERS

It is not known whether this drug is excreted in human milk. Because many drugs are excreted in human milk, caution should be exercised when lidocaine is administered to a nursing woman.

PEDIATRIC USE

Dosage in children should be reduced commensurate with age, body weight and physical conditions. See DOSAGE AND ADMINISTRATION.

ADVERSE REACTIONS

Adverse experiences following the administration of lidocaine are similar in nature to those observed with other amide local anesthetic agents. These adverse experiences are, in general, dose-related and may result from high plasma levels caused by excessive dosage or rapid absorption, or may result from a hypersensitivity, idiosyncrasy or diminished tolerance on the part of the patient. Serious adverse experiences are generally systemic in nature. The following types are those most commonly reported:

Central nervous system

CNS manifestations are excitatory and/or depressant and may be characterized by lightheadedness, nervousness, apprehension, euphoria, confusion, dizziness, drowsiness, tinnitus, blurred or double vision, vomiting, sensations of heat, cold or numbness, twitching, tremors, convulsions, unconsciousness, respiratory depression and arrest. The excitatory manifestations may be very brief or may not occur at all, in which case the first manifestation of toxicity may be drowsiness merging into unconsciousness and respiratory arrest.

Drowsiness following the administration of lidocaine is usually an early sign of a high blood level of the drug and may occur as a consequence of rapid absorption.

Cardiovascular system:

Cardiovascular manifestations are usually depressant and are characterized by bradycardia, hypotension, and cardiovascular collapse, which may lead to cardiac arrest.

Allergic:

Allergic reactions are characterized by cutaneous lesions, urticaria, edema or anaphylactoid reactions. Allergic reactions may occur as a result of sensitivity either to the local anesthetic agent or to other ingredients in the formulation. Allergic reactions as a result of sensitivity to lidocaine are extremely rare and, if they occur, should be managed by conventional means. The detection of sensitivity by skin testing is of doubtful value.

OVERDOSAGE

Acute emergencies from local anesthetics are generally related to high plasma levels encountered during therapeutic use of local anesthetics. (See ADVERSE REACTIONS, WARNINGS, and PRECAUTIONS)

Management of Local Anesthetic Emergencies

The first consideration is prevention, best accomplished by careful and constant monitoring of cardiovascular and respiratory vital signs and the patient’s state of consciousness after each local anesthetic administration. At the first sign of change, oxygen should be administered.

The first steps in the management of convulsions consist of immediate attention to the maintenance of a patent airway and assisted or controlled ventilation with oxygen and a delivery system capable of permitting immediate positive airway pressure by mask. Immediately after the institution of these ventilatory measures, the adequacy of the circulation should be evaluated, keeping in mind that drugs used to treat convulsions sometimes depress the circulation when administered intravenously. Should convulsions persist despite adequate respiratory support, and if the status of the circulation permits, small increments of an ultra-short acting barbiturate (such as thiopental or thiamylal) or a benzodiazepine (such as diazepam) may be administered intravenously. The clinician should be familiar, prior to use of local anesthetics, with these anticonvulsant drugs. Supportive treatment of circulatory depression may require administration of intravenous fluids and, when appropriate, a vasopressor as indicated by the clinical situation (e.g., ephedrine).

If not treated immediately, both convulsions and cardiovascular depression can result in hypoxia, acidosis, bradycardia, arrhythmias and cardiac arrest. If cardiac arrest should occur, standard cardiopulmonary resuscitative measures should be instituted.

Dialysis is of negligible value in the treatment of acute overdosage with lidocaine.

The intravenous LD50of lidocaine HCl in female mice is 26 (21-31) mg/kg and the subcutaneous LD50is 264 (203-304) mg/kg.

DOSAGE & ADMINISTRATION

When lidocaine hydrochloride topical solution 4% is used concomitantly with other products containing lidocaine, the total dose contributed by all formulations must be kept in mind.

The dosage varies and depends upon the area to be anesthetized, vascularity of the tissues, individual tolerance and the technique of anesthesia. The lowest dosage needed to provide effective anesthesia should be administered. Dosages should be reduced for children and for elderly and debilitated patients. The maximum dose should not exceed 4.5 mg/kg (2 mg/lb) of body weight. Although the incidence of adverse effects with lidocaine hydrochloride topical solution 4% is quite low, caution should be exercised particularly when employing large volumes since the incidence of adverse effects is directly proportional to the total dose of local anesthetic agent administered.

The dosages recommended below are for normal healthy adults:

When used as a spray, or when applied by means of cotton applicators or packs, as when instilled into a cavity, the suggested dosage of lidocaine hydrochloride topical solution is 1-5 mL (40-200 mg of lidocaine hydrochloride), i.e., 0.6-3.0 mg/kg or 0.3-1.5 mg/lb of body weight.

NOTE:The solution may be applied with a sterile swab which is discarded after use and never reused under any circumstances. When spraying, transfer the solution from the original container to an atomizer.

Maximum Recommended Dosages:

Normal Healthy Adults:

The maximum recommended dose of lidocaine hydrochloride topical solution should be such that the dose of lidocaine hydrochloride is kept below 300 mg and in any case should never exceed 4.5 mg/kg (2 mg/lb) of body weight.

Children:

It is difficult to recommend a maximum dose of any drug for children since this varies as a function of age and weight. For children of less than ten years who have a normal lean body mass and normal body development, the maximum dose may be determined by the application of one of the standard pediatric drug formulas (e.g., Clark’s rule). For example, in a child of five years weighing 50 lbs., the dose of lidocaine should not exceed 75-100 mg when calculated according to Clark’s rule. In any case, the maximum dose of lidocaine hydrochloride and epinephrine should not exceed 7 mg/kg (3.2 mg/lb) of body weight. When used without epinephrine, the amount of lidocaine hydrochloride administered should be such that the dose is kept below 300 mg and in any case should not exceed 4.5 mg/kg (2 mg/lb) of body weight.

HOW SUPPLIED

Lidocaine Hydrochloride Topical Solution, USP 4%

The 4% topical solution is supplied as a clear, colorless solution free from visible particulate matter.

NDC 10135-736-51: Bottle of 50 mL

Store at 20° to 25°C (68° to 77°F). [See USP Controlled Room Temperature.]

All trademarks are the property of their respective owners.

Manufactured for/ Distriubted by:

Marlex Pharmaceuticals, Inc.

New Castle, DE 19720

Rev. 05/22 NP

PACKAGE LABEL.PRINCIPAL DISPLAY PANEL

Lidocaine Hydrochloride Topical Solution, USP 4%

NDC 10135-736-51: Bottle of 50 mL

Rx Only

PACKAGE CARTON. PRINCIPAL DISPLAY PANEL

Lidocaine Hydrochloride Topical Solution, USP 4%

NDC 10135-736-51: Bottle of 50 mL

Rx Only